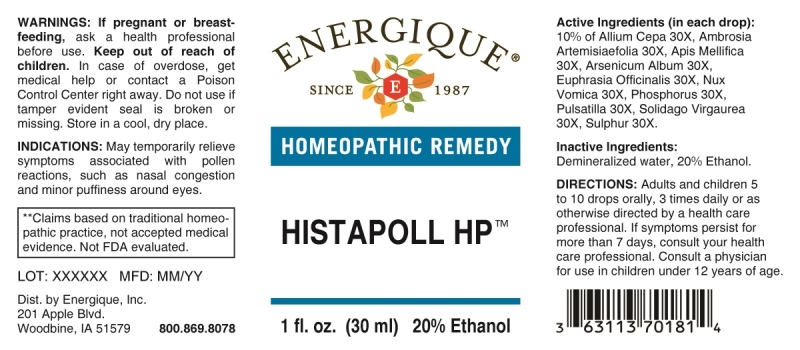 DRUG LABEL: Histapoll HP
NDC: 44911-0581 | Form: LIQUID
Manufacturer: Energique, Inc.
Category: homeopathic | Type: HUMAN OTC DRUG LABEL
Date: 20230421

ACTIVE INGREDIENTS: ONION 30 [hp_X]/1 mL; AMBROSIA ARTEMISIIFOLIA 30 [hp_X]/1 mL; APIS MELLIFERA 30 [hp_X]/1 mL; ARSENIC TRIOXIDE 30 [hp_X]/1 mL; EUPHRASIA STRICTA 30 [hp_X]/1 mL; STRYCHNOS NUX-VOMICA SEED 30 [hp_X]/1 mL; PHOSPHORUS 30 [hp_X]/1 mL; PULSATILLA VULGARIS WHOLE 30 [hp_X]/1 mL; SOLIDAGO VIRGAUREA FLOWERING TOP 30 [hp_X]/1 mL; SULFUR 30 [hp_X]/1 mL
INACTIVE INGREDIENTS: WATER; ALCOHOL

DRUG FACTS:

ACTIVE INGREDIENTS:

(in each drop): 10% Allium Cepa 30X, Ambrosia Artemisiaefolia 30X, Apis Mellifica 30X, Arsenicum Album 30X, Euphrasia Officinalis 30X, Nux Vomica 30X, Phosphorus 30X, Pulsatilla 30X, Solidago Virgaurea 30X, Sulphur 30X.

PURPOSE:

May temporarily relieve symptoms associated with pollen reactions, such as nasal congestion and minor puffiness around eyes.**

**Claims based on traditional homeopathic practice, not accepted medical evidence. Not FDA evaluated.

WARNINGS:

If pregnant or breast-feeding, ask a health professional before use.

Keep out of reach of children. In case of overdose, get medical help or contact a Poison Control center right away.

Do not use if tamper evident seal is broken or missing.

Store in a cool, dry place.

KEEP OUT OF REACH OF CHILDREN:

In case of overdose, get medical help or contact a Poison Control center right away.

DIRECTIONS:

Adults and children 5 to 10 drops orally, 3 times daily or as otherwise directed by a health care professional. If symptoms persist for more than 7 days, consult your health care professional. Consult a physician for use in children under 12 years of age.

INDICATIONS:

May temporarily relieve symptoms associated with pollen reactions, such as nasal congestion and minor puffiness around eyes.**

**Claims based on traditional homeopathic practice, not accepted medical evidence. Not FDA evaluated.

INACTIVE INGREDIENTS:

Demineralized water, 20% Ethanol.

QUESTIONS:

Dist. by Energique, Inc.

201 Apple Blvd.

Woodbine, IA 51579 800.869.8078

PACKAGE DISPLAY LABEL:

ENERGIQUE

SINCE 1987

HOMEOPATHIC REMEDY

HISTAPOLL HP

1 fl. oz. (30 ml)